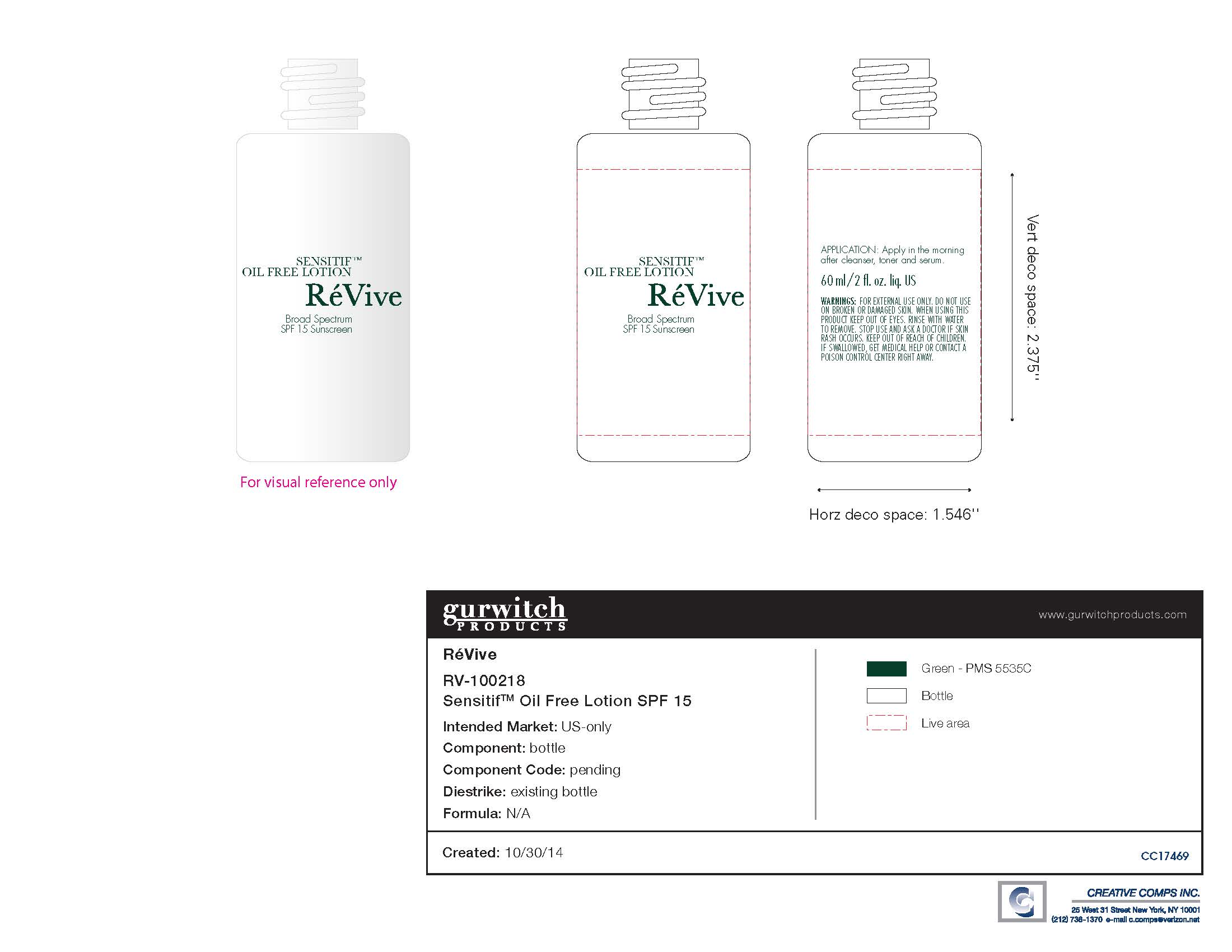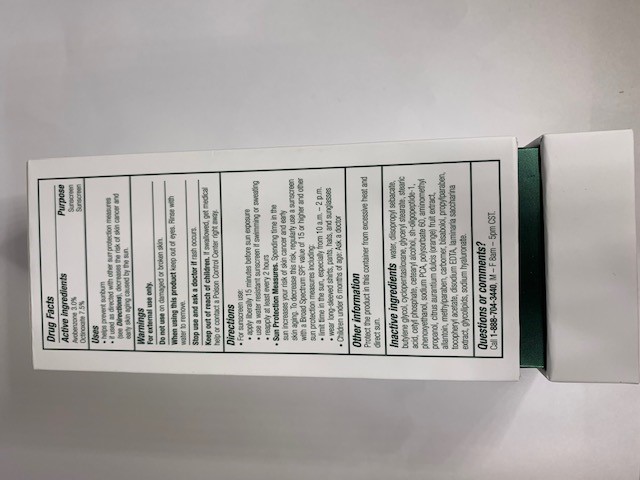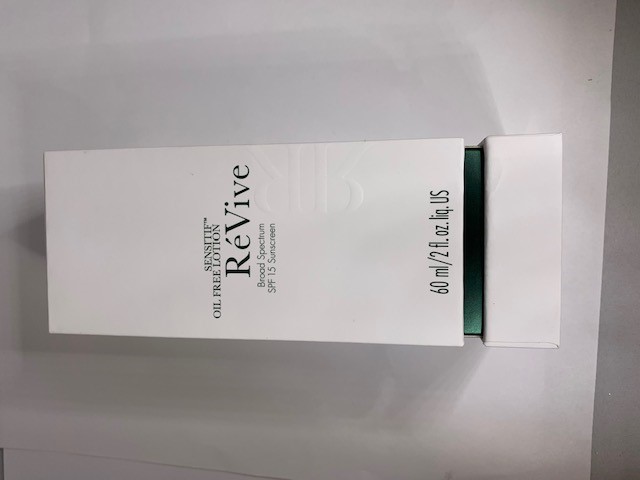 DRUG LABEL: MOISTURIZER
NDC: 61354-032 | Form: CREAM
Manufacturer: OXYGEN DEVELOPMENT, LLC
Category: otc | Type: HUMAN OTC DRUG LABEL
Date: 20230210

ACTIVE INGREDIENTS: OCTINOXATE 7.49 mg/100 mg; AVOBENZONE 3 mg/100 mg
INACTIVE INGREDIENTS: DIISOPROPYL SEBACATE; BUTYLENE GLYCOL; CYCLOMETHICONE 5; GLYCERYL MONOSTEARATE; STEARIC ACID; CETYL PHOSPHATE; CETOSTEARYL ALCOHOL; PHENOXYETHANOL; WATER

SENSITF OIL FREE LOTION REVIVE BROAD SPECTRUM SPF 15 SUNSCREEN

Active Ingredients

Avobenzone 3.0%, Octinoxate 7.5%.

Purpose

Sunscreen

Uses

- Helps prevent sunburn.
- If used as directed with other sun protection measures (see Directions), decreases the risk of skin cancer and early skin aging caused by the sun.

Warnings

For external use only.

Do Not Use on damaged or broken skin.

When using this product keep out of eyes. Rinse with water to remove.

Stop use

Stop use and ask a doctor if rash occurs.

Keep out of reach of children. If swallowed, get medical help or contact a Posion Contorl Center right away.

Directions

- For suncreen use:
- Apply liberally 15 minutes before sun exposure
- Use a water resistant sunscreen if swimming or sweating.
- Reapply at least every 2 hours.
- Sun Protection Measures. Spending time in the sun increases your risk of skin cancer and early skin aging. To decrease this risk, regularly use a sunscreen with a Broad Spectrum SPF value of 15 or higher and other sun protection measures including:
- Limit time in the sun, especially from 10 a.m. - 2p.m.
- Wear long-sleeved shirts, pants, hats and sunglasses
- Children under 6 months of age: Ask a doctor.

Other Information

Protect the product in this container from excessive heat and direct sun.

Inactive Ingredients

Water, diisopropyl sebacate, butylene gycol, cyclopentasiloxane, glyceryl stearate, stearic acid, cetyl phosphate, cetearyl alcohol, sh-oligopeptide-1, phenoxyethanol, sodium PCA, polysorbate 60, aminomethyl propanol, citrus aurantium dulcis (orange) fruit extract, allantoin, methylparaben, carbomer, bisabolol, propylparaben, tocopheryl acetate, disodium EDTA, laminaria saccharina extract, glycolipids, sodium hyaluronate.

Primary package

60 ml 61354-032-01

Secondary package

60ml, 61354-032-01